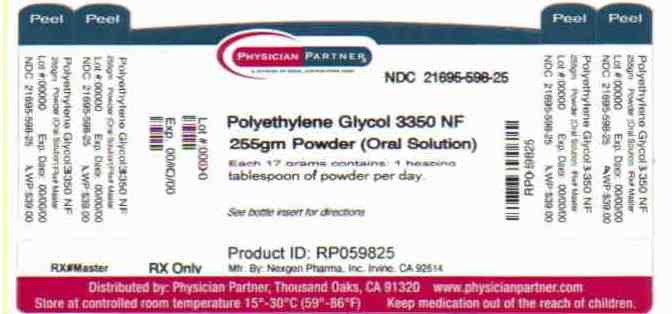 DRUG LABEL: Polyethylene Glycol 3350, NF Powder for Solution, Laxative
NDC: 21695-598 | Form: POWDER, FOR SOLUTION
Manufacturer: Rebel Distributors Corp
Category: otc | Type: HUMAN OTC DRUG LABEL
Date: 20101201

ACTIVE INGREDIENTS: POLYETHYLENE GLYCOL 3350 17 g/1 g
INACTIVE INGREDIENTS: AIR

Drug Facts

Active ingredient

Polyethylene Glycol 3350, 17g (cap filled to the top)

Purpose

Laxative

Uses

- relieves occasional constipation (irregularity)
- generally produces a bowel movement in 1 to 3 days

Warnings

Allergy alert: Do not use If you are allergic to polyethylene glycol

Do not use if you have kidney disease, except under the advice and supervision of a doctor

Ask a doctor before use if you have

- nausea, vomiting or abdominal pain
- a sudden change in bowel habits that lasts over 2 weeks
- irritable bowel syndrome

Ask a doctor or pharmacist before use if you are taking a prescription drug

When using this product you may have loose, watery, more frequent stools

Stop use and ask a doctor if

- you have rectal bleeding or your nausea, bloating, cramping or abdominal pain gets worse. These may be signs of a serious condition.
- you get diarrhea
- you need to use a laxative for longer than 1 week

If pregnant or breast-feeding, ask a health professional before use.

Keep out of reach of children. In case of overdose, get medical help or contact a Poison Control Center right away.

Directions

- do not take more than directed unless advised by your doctor
- The bottle top is a measuring cup designed to contain 17 grams of powder when filled to the top rim.
- adults and children 17 years of age and older
  - fill to the top of the bottle cap which will provide the correct dose (17 g)
  - stir and dissolve in any 4 to 8 ounces of beverage (cold, hot or room temperature) then drink.
  - use once a day
  - use no more than 7 days
- children 16 years of age or younger, ask a doctor

Other Information

- Store at 20O - 25O C (68O - 77O F)
- tamper-evident: do not use if foil seal under cap, printed with “SEALED FOR YOUR PROTECTION” is missing, open or broken.

Inactive ingredients

None

Questions or Comments?

For serious adverse events call:

1-888-710-0006